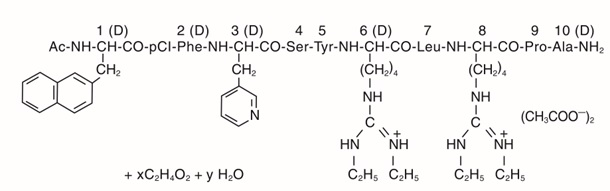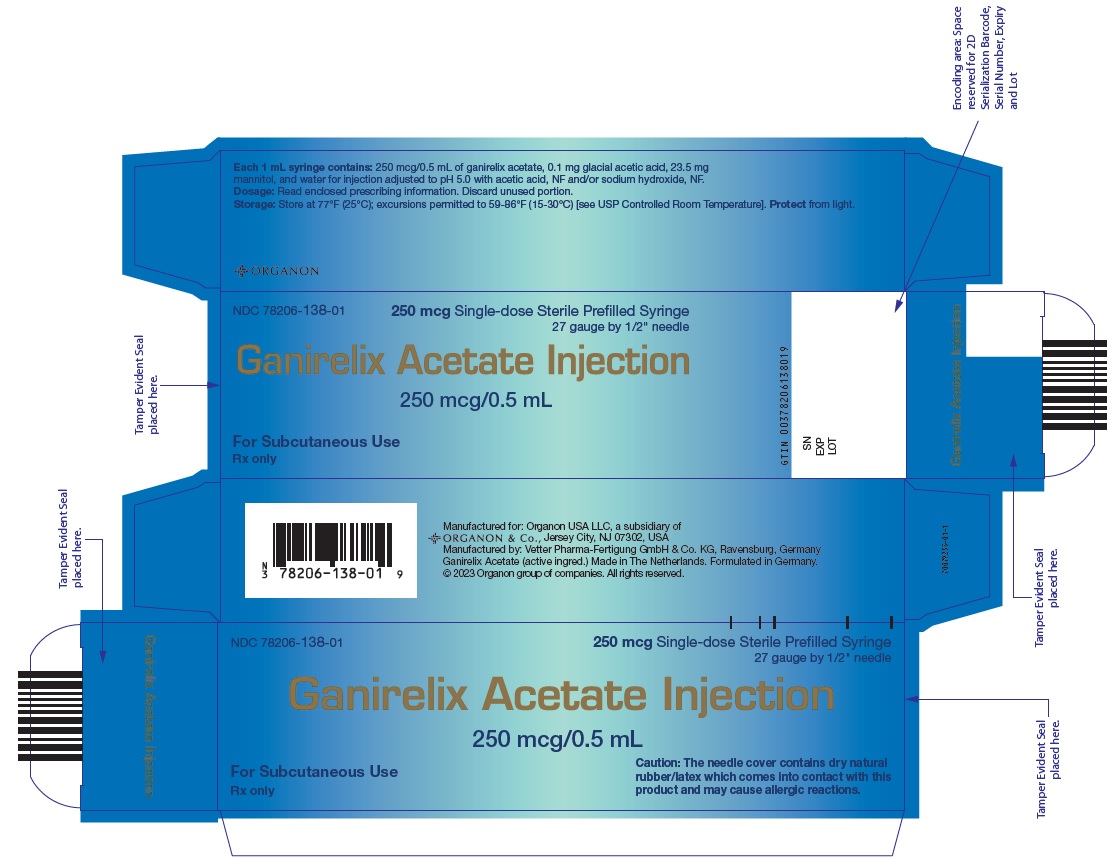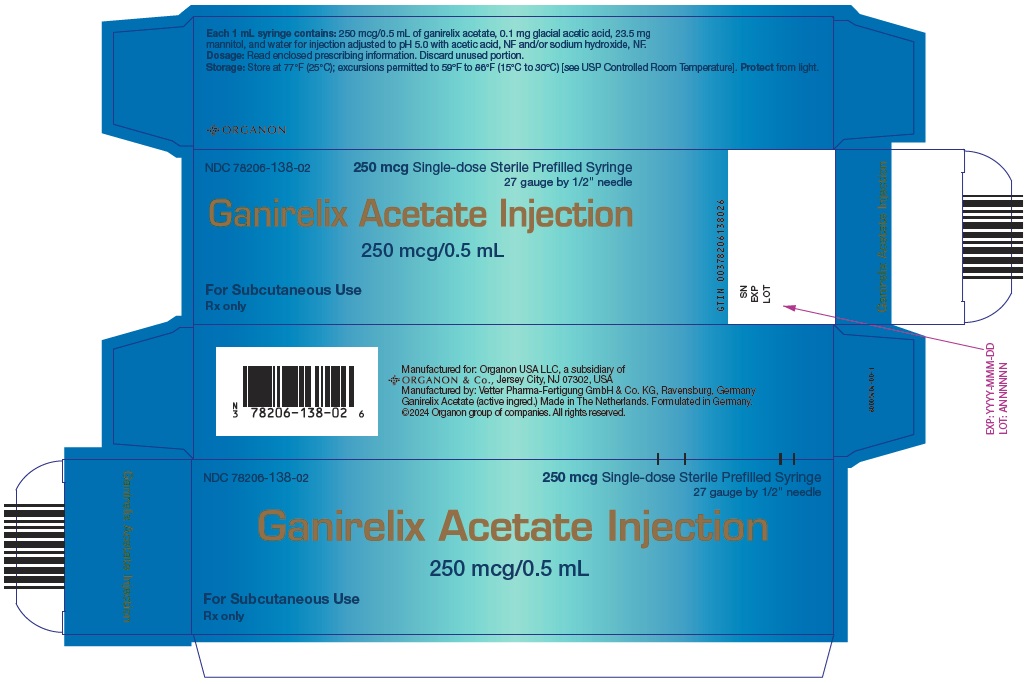 DRUG LABEL: Ganirelix Acetate
NDC: 78206-138 | Form: INJECTION, SOLUTION
Manufacturer: Organon LLC
Category: prescription | Type: HUMAN PRESCRIPTION DRUG LABEL
Date: 20251113

ACTIVE INGREDIENTS: Ganirelix Acetate 250 ug/0.5 mL
INACTIVE INGREDIENTS: mannitol 23.5 mg/0.5 mL; water; acetic acid 0.1 mg/0.5 mL; sodium hydroxide

Ganirelix Acetate Injection

FOR SUBCUTANEOUS USE ONLY

DESCRIPTION

Ganirelix Acetate Injection is a synthetic decapeptide with high antagonistic activity against naturally occurring gonadotropin-releasing hormone (GnRH). Ganirelix Acetate is derived from native GnRH with substitutions of amino acids at positions 1, 2, 3, 6, 8, and 10 to form the following molecular formula of the peptide: N-acetyl-3-(2-naphthyl)-D-alanyl-4-chloro-D-phenylalanyl-3-(3-pyridyl)-D-alanyl-L-seryl-L-tyrosyl-N^9,N^10-diethyl-D-homoarginyl-L-leucyl-N^9,N^10-diethyl-L-homoarginyl-L-prolyl-D-alanylamide acetate. The molecular weight for Ganirelix Acetate is 1570.4 as an anhydrous free base. The structural formula is as follows:

Ganirelix Acetate

Ganirelix Acetate Injection is supplied as a colorless, sterile, ready-to-use, aqueous solution intended for SUBCUTANEOUS administration only. Each single dose, sterile, prefilled syringe contains 250 mcg/0.5 mL of Ganirelix Acetate, 0.1 mg glacial acetic acid, 23.5 mg mannitol, and water for injection adjusted to pH 5.0 with acetic acid, NF and/or sodium hydroxide, NF.

CLINICAL PHARMACOLOGY

The pulsatile release of GnRH stimulates the synthesis and secretion of luteinizing hormone (LH) and follicle-stimulating hormone (FSH). The frequency of LH pulses in the mid and late follicular phase is approximately 1 pulse per hour. These pulses can be detected as transient rises in serum LH. At midcycle, a large increase in GnRH release results in an LH surge. The midcycle LH surge initiates several physiologic actions including: ovulation, resumption of meiosis in the oocyte, and luteinization. Luteinization results in a rise in serum progesterone with an accompanying decrease in estradiol levels.

Ganirelix Acetate acts by competitively blocking the GnRH receptors on the pituitary gonadotroph and subsequent transduction pathway. It induces a rapid, reversible suppression of gonadotropin secretion. The suppression of pituitary LH secretion by Ganirelix Acetate is more pronounced than that of FSH. An initial release of endogenous gonadotropins has not been detected with Ganirelix Acetate, which is consistent with an antagonist effect. Upon discontinuation of Ganirelix Acetate, pituitary LH and FSH levels are fully recovered within 48 hours.

Pharmacokinetics

The pharmacokinetic parameters of single and multiple injections of Ganirelix Acetate Injection in healthy adult females are summarized in Table I. Steady-state serum concentrations are reached after 3 days of treatment. The pharmacokinetics of Ganirelix Acetate are dose-proportional in the dose range of 125 to 500 mcg.

TABLE I: Mean (SD) pharmacokinetic parameters of 250 mcg of Ganirelix Acetate following a single subcutaneous (SC) injection (n=15) and daily SC injections (n=15) for seven days.
 | tmax h | t½ h | Cmax ng/mL | AUC ng∙h/mL | CL/F L/h | Vd/F L
Ganirelix Acetate single dose | 1.1 (0.3) | 12.8 (4.3) | 14.8 (3.2) | 96 (12) | 2.4 (0.2) [Based on intravenous administration] | 43.7 (11.4)
Ganirelix Acetate multiple dose | 1.1 (0.2) | 16.2 (1.6) | 11.2 (2.4) | 77.1 (9.8) | 3.3 (0.4) | 76.5 (10.3)
tmax Time to maximum concentration
t½ Elimination half-life
Cmax Maximum serum concentration
AUC Area under the curve; Single dose: AUC0–∞; multiple dose: AUC0–24
Vd Volume of distribution
CL Clearance = Dose/AUC0–∞
F Absolute bioavailability

Absorption

Ganirelix Acetate is rapidly absorbed following subcutaneous injection with maximum serum concentrations reached approximately one hour after dosing. The mean absolute bioavailability of Ganirelix Acetate following a single 250 mcg subcutaneous injection to healthy female volunteers is 91.1%.

Distribution

The mean (SD) volume of distribution of Ganirelix Acetate in healthy females following intravenous administration of a single 250-mcg dose is 43.7 (11.4) liters (L). In vitro protein binding to human plasma is 81.9%.

Metabolism

Following single-dose intravenous administration of radiolabeled Ganirelix Acetate to healthy female volunteers, Ganirelix Acetate is the major compound present in the plasma (50–70% of total radioactivity in the plasma) up to 4 hours and urine (17.1–18.4% of administered dose) up to 24 hours. Ganirelix Acetate is not found in the feces. The 1–4 peptide and 1–6 peptide of Ganirelix Acetate are the primary metabolites observed in the feces.

Excretion

On average, 97.2% of the total radiolabeled Ganirelix Acetate dose is recovered in the feces and urine (75.1% and 22.1%, respectively) over 288 h following intravenous single dose administration of 1 mg [^14C]-Ganirelix Acetate. Urinary excretion is virtually complete in 24 h, whereas fecal excretion starts to plateau 192 h after dosing.

Special Populations

The pharmacokinetics of Ganirelix Acetate Injection have not been determined in special populations such as geriatric, pediatric, renally impaired and hepatically impaired patients (see PRECAUTIONS).

Drug-Drug Interactions

Formal in vivo or in vitro drug-drug interaction studies have not been conducted (see PRECAUTIONS). Since Ganirelix Acetate can suppress the secretion of pituitary gonadotropins, dose adjustments of exogenous gonadotropins may be necessary when used during controlled ovarian hyperstimulation (COH).

Clinical Studies

The efficacy of Ganirelix Acetate Injection was established in two adequate and well-controlled clinical studies which included women with normal endocrine and pelvic ultrasound parameters. The studies intended to exclude subjects with polycystic ovary syndrome (PCOS) and subjects with low or no ovarian reserve. One cycle of study medication was administered to each randomized subject. For both studies, the administration of exogenous recombinant FSH [Follistim® (follitropin beta for injection)] 150 IU daily was initiated on the morning of Day 2 or 3 of a natural menstrual cycle. Ganirelix Acetate Injection was administered on the morning of Day 7 or 8 (Day 6 of recombinant FSH administration). The dose of recombinant FSH administered was adjusted according to individual responses starting on the day of initiation of Ganirelix Acetate. Both recombinant FSH and Ganirelix Acetate were continued daily until at least three follicles were 17 mm or greater in diameter at which time hCG [Pregnyl® (chorionic gonadotropin for injection, USP)] was administered. Following hCG administration, Ganirelix Acetate and recombinant FSH administration were discontinued. Oocyte retrieval, followed by in vitro fertilization (IVF) or intracytoplasmic sperm injection (ICSI), was subsequently performed.

In a multicenter, double-blind, randomized, dose-finding study, the safety and efficacy of Ganirelix Acetate Injection were evaluated for the prevention of LH surges in women undergoing COH with recombinant FSH. Ganirelix Acetate Injection doses ranging from 62.5 mcg to 2000 mcg and recombinant FSH were administered to 332 patients undergoing COH for IVF (see TABLE II). Median serum LH on the day of hCG administration decreased with increasing doses of Ganirelix Acetate. Median serum E2 (17β-estradiol) on the day of hCG administration was 1475, 1110, and 1160 pg/mL for the 62.5-, 125-, and 250-mcg doses, respectively. Lower peak serum E2 levels of 823, 703, and 441 pg/mL were seen at higher doses of Ganirelix Acetate 500, 1000, and 2000 mcg, respectively. The highest pregnancy and implantation rates were achieved with the 250-mcg dose of Ganirelix Acetate Injection as summarized in Table II.

TABLE II: Results from the multicenter, double-blind, randomized, dose-finding study to assess the efficacy of Ganirelix Acetate Injection to prevent premature LH surges in women undergoing COH with recombinant FSH.
 | Daily dose (mcg) of Ganirelix Acetate Injection
 | 62.5 mcg | 125 mcg | 250 mcg | 500 mcg | 1000 mcg | 2000 mcg
No. subjects receiving Ganirelix Acetate | 31 | 66 | 70 | 69 | 66 | 30
No. subjects with ET [ET: Embryo Transfer] | 27 | 61 | 62 | 54 | 61 | 27
No. of subjects with LH rise ≥ 10 mIU/mL [Following initiation of Ganirelix Acetate therapy. Includes subjects who have complied with daily injections] | 4 | 6 | 1 | 0 | 0 | 0
Serum LH (mIU/mL) on day of hCG [Median values] | 3.6 | 2.5 | 1.7 | 1.0 | 0.6 | 0.3
5th–95th percentiles | 0.6–19.9 | 0.6–11.4 | < 0.25–6.4 | 0.4–4.7 | < 0.25–2.2 | < 0.25–0.8
Serum E2 (pg/mL) on day of hCG | 1475 | 1110 | 1160 | 823 | 703 | 441
5th–95th percentiles | 645–3720 | 424–3780 | 384–3910 | 279–2720 | 284–2360 | 166–1940
Vital pregnancy rate [As evidenced by ultrasound at 5–6 weeks following ET]
per attempt, n (%) | 7 (22.6) | 17 (25.8) | 25 (35.7) | 8 (11.6) | 9 (13.6) | 2 (6.7)
per transfer, n (%) | 7 (25.9) | 17 (27.9) | 25 (40.3) | 8 (14.8) | 9 (14.8) | 2 (7.4)
Implantation rate (%) [Mean (standard deviation)] | 14.2 (26.8) | 16.3 (30.5) | 21.9 (30.6) | 9.0 (23.7) | 8.5 (21.7) | 4.9 (20.1)
(Protocol 38602)

Transient LH rises alone were not deleterious to achieving pregnancy with Ganirelix Acetate at doses of 125 mcg (3/6 subjects) and 250 mcg (1/1 subjects). In addition, none of the subjects with LH rises ≥ 10 mIU/mL had premature luteinization indicated by a serum progesterone above 2 ng/mL.

A multicenter, open-label, randomized study was conducted to assess the efficacy and safety of Ganirelix Acetate Injection in women undergoing COH. Follicular phase treatment with Ganirelix Acetate 250 mcg was studied using a luteal phase GnRH agonist as a reference treatment. A total of 463 subjects were treated with Ganirelix Acetate by subcutaneous injection once daily starting on Day 6 of recombinant FSH treatment. Recombinant FSH was maintained at 150 IU for the first 5 days of ovarian stimulation and was then adjusted by the investigator on the sixth day of gonadotropin use according to individual responses. The results for the Ganirelix Acetate arm are summarized in Table III.

TABLE III: Results from the multicenter, open-label, randomized study to assess the efficacy and safety of Ganirelix Acetate Injection in women undergoing COH.
 | Ganirelix Acetate 250 mcg
No. subjects treated | 463
Duration of GnRH analog (days) [Restricted to subjects with hCG injection] , [Mean (standard deviation)] | 5.4 (2.0)
Duration of recombinant FSH (days), | 9.6 (2.0)
Serum E2 (pg/mL) on day of hCG [Median values] 5th–95th percentiles | 1190 373–3105
Serum LH (mIU/mL) on day of hCG 5th–95th percentiles | 1.6 0.6–6.9
No. of subjects with LH rise≥10 mIU/mL [Following initiation of Ganirelix Acetate therapy] | 13
No. of follicles > 11 mm, | 10.7 (5.3)
No. of subjects with oocyte retrieval | 440
No. of oocytes | 8.7 (5.6)
Fertilization rate | 62.1%
No. subjects with ET [ET: Embryo Transfer] | 399
No. of embryos transferred | 2.2 (0.6)
No. of embryos | 6.0 (4.5)
Ongoing pregnancy rate [As evidenced by ultrasound at 12–16 weeks following ET] ,
per attempt, n (%) [Includes one patient who achieved pregnancy with intrauterine induction] | 94 (20.3)
per transfer, n (%) | 93 (23.3)
Implantation rate (%) | 15.7 (29)
(Protocol 38607)
Some centers were limited to the transfer of ≤ 2 embryos based on local practice standards

The mean number of days of Ganirelix Acetate treatment was 5.4 (2–14).

LH Surges

The midcycle LH surge initiates several physiologic actions including: ovulation, resumption of meiosis in the oocyte, and luteinization. In 463 subjects administered Ganirelix Acetate Injection 250 mcg, a premature LH surge prior to hCG administration, (LH rise ≥ 10 mIU/mL with a significant rise in serum progesterone > 2 ng/mL, or a significant decline in serum estradiol) occurred in less than 1% of subjects.

INDICATIONS AND USAGE

Ganirelix Acetate Injection is indicated for the inhibition of premature LH surges in women undergoing controlled ovarian hyperstimulation.

CONTRAINDICATIONS

Ganirelix Acetate Injection is contraindicated under the following conditions:

- Known hypersensitivity to Ganirelix Acetate or to any of its components including dry natural rubber/latex which may be contained in the rigid needle shield (see HOW SUPPLIED).
- Known hypersensitivity to GnRH or any other GnRH analog.
- Known or suspected pregnancy (see PRECAUTIONS).

WARNINGS

Ganirelix Acetate Injection should be prescribed by physicians who are experienced in infertility treatment. Before starting treatment with Ganirelix Acetate, pregnancy must be excluded. Safe use of Ganirelix Acetate during pregnancy has not been established (see CONTRAINDICATIONS and PRECAUTIONS).

PRECAUTIONS

General

Special care should be taken in women with signs and symptoms of active allergic conditions. Cases of hypersensitivity reactions (both generalized and local), including anaphylaxis (including anaphylactic shock), angioedema and urticaria, have been reported with Ganirelix Acetate, as early as with the first dose, during post-marketing surveillance (see ADVERSE REACTIONS). If a hypersensitivity reaction is suspected, Ganirelix Acetate should be discontinued and appropriate treatment administered. In the absence of clinical experience, Ganirelix Acetate treatment is not advised in women with severe allergic conditions.

The rigid needle shield of this product may contain dry natural rubber/latex which comes into contact with this product and may cause allergic reactions (see CONTRAINDICATIONS and HOW SUPPLIED).

Information for Patients

Prior to therapy with Ganirelix Acetate Injection, patients should be informed of the duration of treatment and monitoring procedures that will be required. The risk of possible adverse reactions should be discussed (see ADVERSE REACTIONS).

Ganirelix Acetate should not be prescribed if the patient is pregnant.

Laboratory Tests

A neutrophil count ≥ 8.3 (x 10^9/L) was noted in 11.9% (up to 16.8 x 10^9/L) of all subjects treated within the adequate and well-controlled clinical trials. In addition, downward shifts within the Ganirelix Acetate Injection group were observed for hematocrit and total bilirubin. The clinical significance of these findings was not determined.

Drug Interactions

No formal drug-drug interaction studies have been performed.

Carcinogenesis and Mutagenesis, Impairment of Fertility

Long-term toxicity studies in animals have not been performed with Ganirelix Acetate Injection to evaluate the carcinogenic potential of the drug. Ganirelix Acetate did not induce a mutagenic response in the Ames test (S. typhimurium and E. coli) or produce chromosomal aberrations in in vitro assay using Chinese Hamster Ovary cells.

Pregnancy

Ganirelix Acetate Injection is contraindicated in pregnant women. When administered from Day 7 to near term to pregnant rats and rabbits at doses up to 10 and 30 mcg/day (approximately 0.4 to 3.2 times the human dose based on body surface area), Ganirelix Acetate increased the incidence of litter resorption. There was no increase in fetal abnormalities. No treatment-related changes in fertility, physical, or behavioral characteristics were observed in the offspring of female rats treated with Ganirelix Acetate during pregnancy and lactation.

The effects on fetal resorption are logical consequences of the alteration in hormonal levels brought about by the antigonadotropic properties of this drug and could result in fetal loss in humans. Therefore, this drug should not be used in pregnant women (see CONTRAINDICATIONS).

Nursing Mothers

Ganirelix Acetate Injection should not be used by lactating women. It is not known whether this drug is excreted in human milk.

Geriatric Use

Clinical studies with Ganirelix Acetate Injection did not include a sufficient number of subjects aged 65 and over.

ADVERSE REACTIONS

The safety of Ganirelix Acetate Injection was evaluated in two randomized, parallel-group, multicenter controlled clinical studies. Treatment duration for Ganirelix Acetate ranged from 1 to 14 days. Table IV represents adverse events (AEs) from first day of Ganirelix Acetate administration until confirmation of pregnancy by ultrasound at an incidence of ≥ 1% in Ganirelix Acetate-treated subjects without regard to causality.

TABLE IV: Incidence of common adverse events (Incidence ≥ 1% in Ganirelix Acetate-treated subjects). Completed controlled clinical studies (All-subjects-treated group).
Adverse Events Occurring in ≥ 1% | Ganirelix Acetate N=794 % (n)
Abdominal Pain (gynecological) | 4.8 (38)
Death Fetal | 3.7 (29)
Headache | 3.0 (24)
Ovarian Hyperstimulation Syndrome | 2.4 (19)
Vaginal Bleeding | 1.8 (14)
Injection Site Reaction | 1.1 (9)
Nausea | 1.1 (9)
Abdominal Pain (gastrointestinal) | 1.0 (8)

During post-marketing surveillance, rare cases of hypersensitivity reactions, including anaphylaxis (including anaphylactic shock), angioedema and urticaria have been reported with Ganirelix Acetate, as early as with the first dose (see PRECAUTIONS).

Congenital Anomalies

An observational study in more than 1000 newborns compared the incidence of congenital anomalies in newborns of women administered Ganirelix Acetate to historical controls of a GnRH agonist. This study demonstrated that the incidence of congenital anomalies in children born after COH treatment in women using Ganirelix Acetate was comparable with that reported after a COH treatment cycle using a GnRH agonist.

The incidence of congenital malformations after some Assisted Reproductive Technologies (ART) [specifically in vitro fertilization (IVF) or intracytoplasmic sperm injection (ICSI)] may be slightly higher than after spontaneous conception. This slightly higher incidence is thought to be related to differences in parental characteristics (e.g., maternal age, maternal and paternal genetic background, sperm characteristics) and to the higher incidence of multi-fetal gestations after IVF or ICSI. The causal relationship between these congenital anomalies and Ganirelix Acetate Injection is unknown.

OVERDOSAGE

There have been no reports of overdosage with Ganirelix Acetate Injection in humans.

DOSAGE AND ADMINISTRATION

After initiating FSH therapy on Day 2 or 3 of the cycle, Ganirelix Acetate Injection 250 mcg may be administered subcutaneously once daily during the mid to late portion of the follicular phase. By taking advantage of endogenous pituitary FSH secretion, the requirement for exogenously administered FSH may be reduced. Treatment with Ganirelix Acetate should be continued daily until the day of hCG administration. When a sufficient number of follicles of adequate size are present, as assessed by ultrasound, final maturation of follicles is induced by administering hCG. The administration of hCG should be withheld in cases where the ovaries are abnormally enlarged on the last day of FSH therapy to reduce the chance of developing OHSS (Ovarian Hyperstimulation Syndrome).

Directions for Using Ganirelix Acetate Injection

1. Ganirelix Acetate Injection is supplied in a single dose, sterile, prefilled syringe and is intended for SUBCUTANEOUS administration only.
2. Air bubble(s) may be seen in the pre-filled syringe. This is expected, and removal of the air bubble(s) is not needed.
3. Wash hands thoroughly with soap and water.
4. The most convenient sites for SUBCUTANEOUS injection are in the abdomen around the navel or upper thigh.
5. The injection site should be swabbed with a disinfectant to remove any surface bacteria. Clean about two inches around the point where the needle will be inserted and let the disinfectant dry for at least one minute before proceeding.
6. With syringe held upward, remove needle cover.
7. Pinch up a large area of skin between the finger and thumb. Vary the injection site a little with each injection.
8. The needle should be inserted at the base of the pinched-up skin at an angle of 45–90° to the skin surface.
9. When the needle is correctly positioned, it will be difficult to draw back on the plunger. If any blood is drawn into the syringe, the needle tip has penetrated a vein or artery. If this happens, withdraw the needle slightly and reposition the needle without removing it from the skin. Alternatively, remove the needle and use a new, sterile, prefilled syringe. Cover the injection site with a swab containing disinfectant and apply pressure; the site should stop bleeding within one or two minutes.
10. Once the needle is correctly placed, depress the plunger slowly and steadily, so the solution is correctly injected and the skin is not damaged.
11. Pull the syringe out quickly and apply pressure to the site with a swab containing disinfectant.
12. Use the sterile, prefilled syringe only once. Discard the unused portion and dispose of it properly.

HOW SUPPLIED

Ganirelix Acetate Injection is supplied in a carton containing one of the following:

Disposable, ready for use, single dose, sterile, prefilled 1 mL glass syringes containing 250 mcg/0.5 mL aqueous solution of Ganirelix Acetate closed with a rubber piston that does not contain latex. Each Ganirelix Acetate sterile, prefilled syringe is affixed with a 27 gauge × ½-inch needle closed by a needle shield of dry natural rubber/latex which comes into contact with this product. (See CONTRAINDICATIONS and PRECAUTIONS, General.), NDC No. 78206-138-01

Disposable, ready to use, single dose, sterile, prefilled 1 mL glass syringe containing 250 mcg/0.5 mL aqueous solution of Ganirelix Acetate closed with a plunger stopper. Each Ganirelix Acetate sterile, prefilled syringe is affixed with a 27 gauge x ½ inch staked needle closed by a rigid needle shield (RNS) not made with natural rubber latex, NDC No. 78206-138-02.

Storage

Store at 77°F (25°C); excursions permitted to 59°F to 86°F (15°C to 30°C) [see USP Controlled Room Temperature]. Protect from light.

Manufactured for: Organon USA LLC, a subsidiary of
ORGANON & Co.,
Jersey City, NJ 07302, USA

For patent information: www.organon.com/our-solutions/patent/

© 2024 Organon group of companies. All rights reserved.

Revised: 2/2024

uspi-og8761-soi-2402r002

PRINCIPAL DISPLAY PANEL - 250 mcg/0.5 mL Syringe Blister Pack Carton

NDC 78206-138-01

250 mcg Single-dose Sterile Prefilled Syringe
27 gauge by 1/2" needle

Ganirelix Acetate Injection

250 mcg/0.5 mL

For Subcutaneous Use
Rx only

Caution: The needle cover contains dry natural
rubber/latex which comes into contact with this
product and may cause allergic reactions.

PRINCIPAL DISPLAY PANEL - 250 mcg/0.5 mL Syringe Blister Pack Carton

NDC 78206-138-02

250 mcg Single-dose Sterile Prefilled Syringe
27 gauge by 1/2" needle

Ganirelix Acetate Injection

250 mcg/0.5 mL

For Subcutaneous Use
Rx only